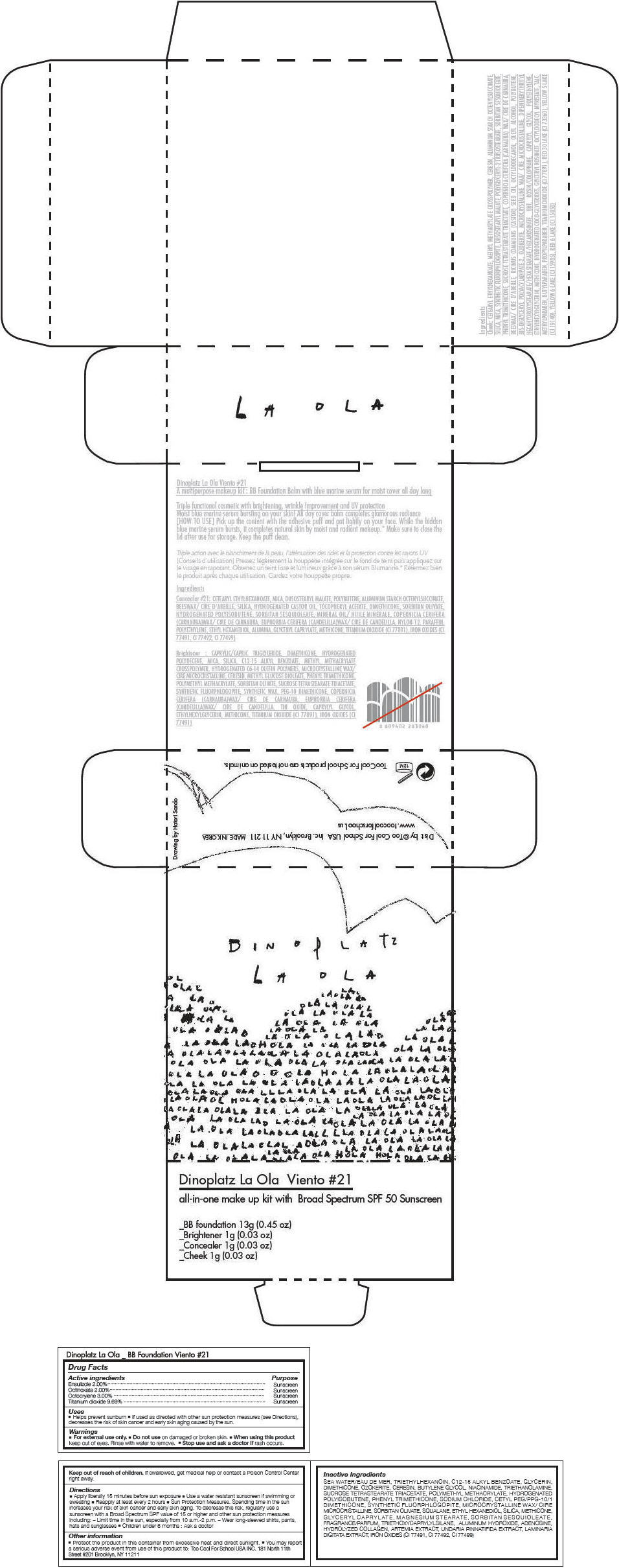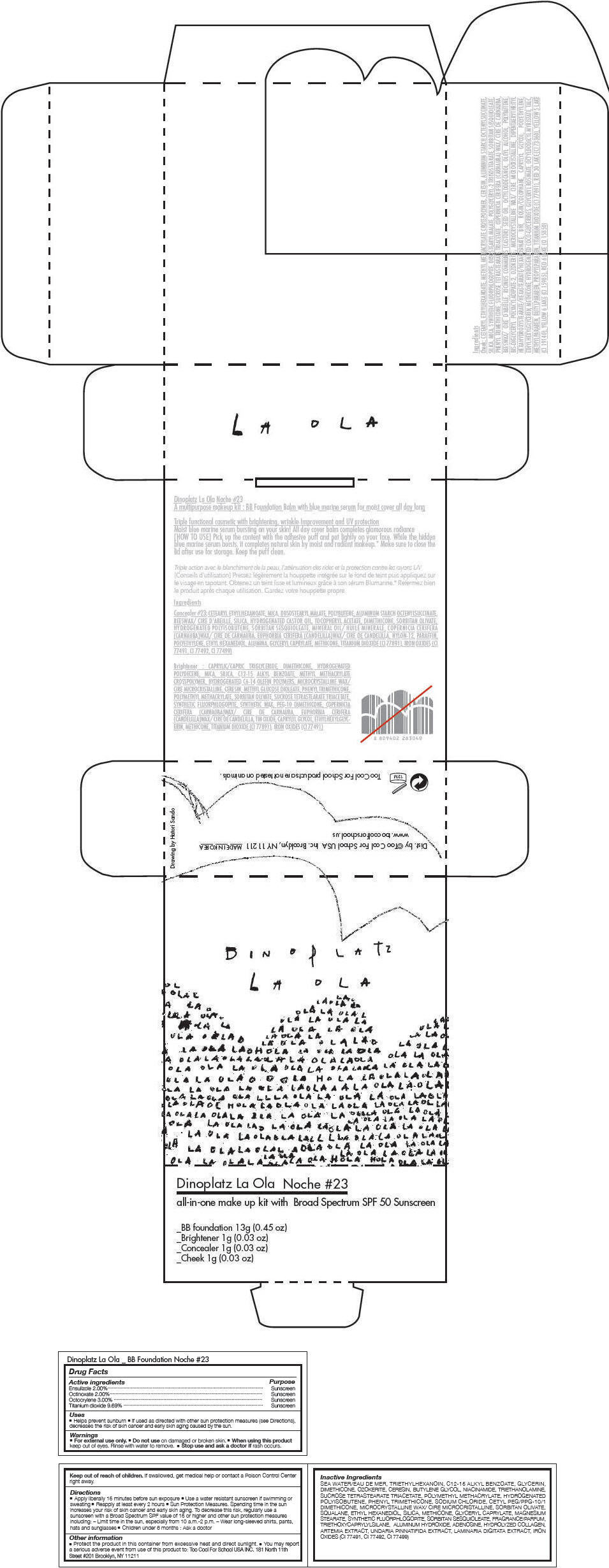 DRUG LABEL: Too Cool For School 
NDC: 69926-008 | Form: KIT | Route: TOPICAL
Manufacturer: Too Cool For School USA, Inc
Category: otc | Type: HUMAN OTC DRUG LABEL
Date: 20150731

ACTIVE INGREDIENTS: ENSULIZOLE 20 mg/1 g; OCTINOXATE 20 mg/1 g; OCTOCRYLENE 30 mg/1 g; TITANIUM DIOXIDE 96.9 mg/1 g
INACTIVE INGREDIENTS: SODIUM CHLORIDE; TRIETHYLHEXANOIN; ALKYL (C12-15) BENZOATE; GLYCERIN; DIMETHICONE; CERESIN; BUTYLENE GLYCOL; NIACINAMIDE; TROLAMINE; SUCROSE TETRASTEARATE TRIACETATE; PHENYL TRIMETHICONE; MICROCRYSTALLINE WAX; SORBITAN OLIVATE; SQUALANE; ETHOHEXADIOL; SILICON DIOXIDE; GLYCERYL CAPRYLATE; MAGNESIUM STEARATE; SORBITAN SESQUIOLEATE; TRIETHOXYCAPRYLYLSILANE; ALUMINUM HYDROXIDE; ADENOSINE; UNDARIA PINNATIFIDA; LAMINARIA DIGITATA; FERRIC OXIDE RED

Too Cool For School
DINOPLATZ La Ola Viento

Drug Facts

ACTIVE INGREDIENT

Active ingredients | Purpose
Ensulizole 2.00% | Sunscreen
Octinoxate 2.00% | Sunscreen
Octocrylene 3.00% | Sunscreen
Titanium dioxide 9.69% | Sunscreen

Uses

- Helps prevent sunburn
- If used as directed with other sun protection measures (see Directions), decreases the risk of skin cancer and early skin aging caused by the sun.

Warnings

- For external use only.

- Do not use on damaged or broken skin.

- When using this product keep out of eyes. Rinse with water to remove.

- Stop use and ask a doctor if rash occurs.

Keep out of reach of children. If swallowed, get medical help or contact a Poison Control Center right away.

Directions

- Apply liberally 15 minutes before sun exposure
- Use a water resistant sunscreen if swimming or sweating
- Reapply at least every 2 hours
- Sun Protection Measures. Spending time in the sun increases your risk of skin cancer and early skin aging. To decrease this risk, regularly use a sunscreen with a Broad Spectrum SPF value of 15 or higher and other sun protection measures including:
  - Limit time in the sun, especially from 10 a.m.-2 p.m.
  - Wear long-sleeved shirts, pants, hats and sunglasses
- Children under 6 months : Ask a doctor

Other information

- Protect the product in this container from excessive heat and direct sunlight.
- You may report a serious adverse event from use of this product to: Too Cool For School USA INC. 181 North 11th Street #201 Brooklyn, NY 11211

Inactive Ingredients

SEA WATER/EAU DE MER, TRIETHYLHEXANOIN, C12-15 ALKYL BENZOATE, GLYCERIN, DIMETHICONE, OZOKERITE, CERESIN, BUTYLENE GLYCOL, NIACINAMIDE, TRIETHANOLAMINE, SUCROSE TETRASTEARATE TRIACETATE, POLYMETHYL METHACRYLATE, HYDROGENATED POLYISOBUTENE, PHENYL TRIMETHICONE, SODIUM CHLORIDE, CETYL PEG/PPG-10/1 DIMETHICONE, SYNTHETIC FLUORPHLOGOPITE, MICROCRYSTALLINE WAX/ CIRE MICROCRISTALLINE, SORBITAN OLIVATE, SQUALANE, ETHYL HEXANEDIOL, SILICA, METHICONE, GLYCERYL CAPRYLATE, MAGNESIUM STEARATE, SORBITAN SESQUIOLEATE, FRAGRANCE/PARFUM, TRIETHOXYCAPRYLYLSILANE, ALUMINUM HYDROXIDE, ADENOSINE, HYDROLYZED COLLAGEN, ARTEMIA EXTRACT, UNDARIA PINNATIFIDA EXTRACT, LAMINARIA DIGITATA EXTRACT, IRON OXIDES (CI 77491, CI 77492, CI 77499)

Dist. by ©Too Cool For School USA Inc. Brooklyn, NY 11211

PRINCIPAL DISPLAY PANEL - #21 Kit Carton

Dinoplatz La Ola Viento #21
all-in-one make up kit with Broad Spectrum SPF 50 Sunscreen

_BB foundation 13g (0.45 oz)
_Brightener 1g (0.03 oz)
_Concealer 1g (0.03 oz)
_Cheek 1g (0.03 oz)

PRINCIPAL DISPLAY PANEL - #23 Kit Carton

Dinoplatz La Ola Noche #23
all-in-one make up kit with Broad Spectrum SPF 50 Sunscreen

_BB foundation 13g (0.45 oz)
_Brightener 1g (0.03 oz)
_Concealer 1g (0.03 oz)
_Cheek 1g (0.03 oz)